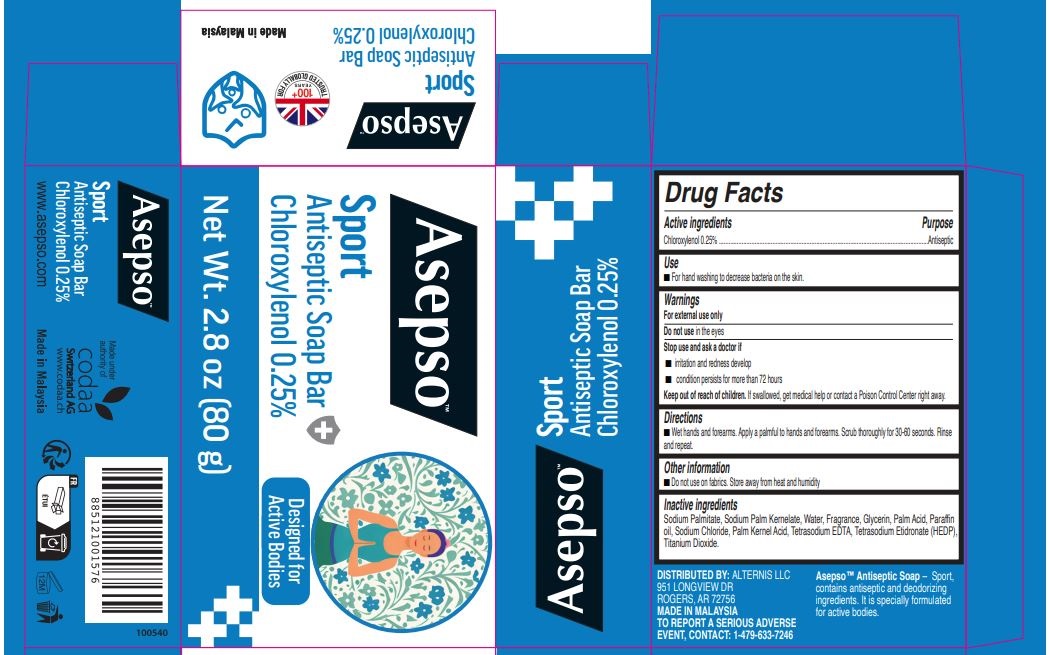 DRUG LABEL: Asepso Sport Antiseptic
NDC: 49698-006 | Form: SOAP
Manufacturer: CODAA SWITZERLAND AG
Category: otc | Type: HUMAN OTC DRUG LABEL
Date: 20231027

ACTIVE INGREDIENTS: CHLOROXYLENOL 2.5 mg/1 g
INACTIVE INGREDIENTS: TITANIUM DIOXIDE; ETIDRONATE TETRASODIUM; SODIUM PALMATE; SODIUM PALM KERNELATE; WATER; GLYCERIN; PALM ACID; MINERAL OIL; SODIUM CHLORIDE; PALM KERNEL ACID; EDETATE SODIUM

Asepso Sport Antiseptic Soap

Active ingredient

Chloroxylenol 0.25%

Purpose

Antiseptic

Use

For hand washing to decrease bacteria on the skin.

Warnings

For external use only

Do not use

in the eyes.

Stop use and ask a doctor if

- irritation and redness develop.
- condition persists for more than 72 hours.

Keep out of reach of children.

If swallowed, get medical help or contact a Poison Control Center right away.

Directions

- Wet hands and forearms.
- Apply to hands and forearms. Scrub thoroughly for 60 seconds.
- Rinse and repeat.

Other information

Do not use on fabrics. Store away from heat and humidity.

Inactive ingredients

Sodium Palmate, Sodium Palm Kernelate, Aqua, Fragrance, Glycerin, Palm Acid, Paraffinum Liquidum, Sodium Chloride, Palm Kernel Acid, Tetrasodium EDTA, CI 77891, Tetrasodium Etidronate (HEDP).